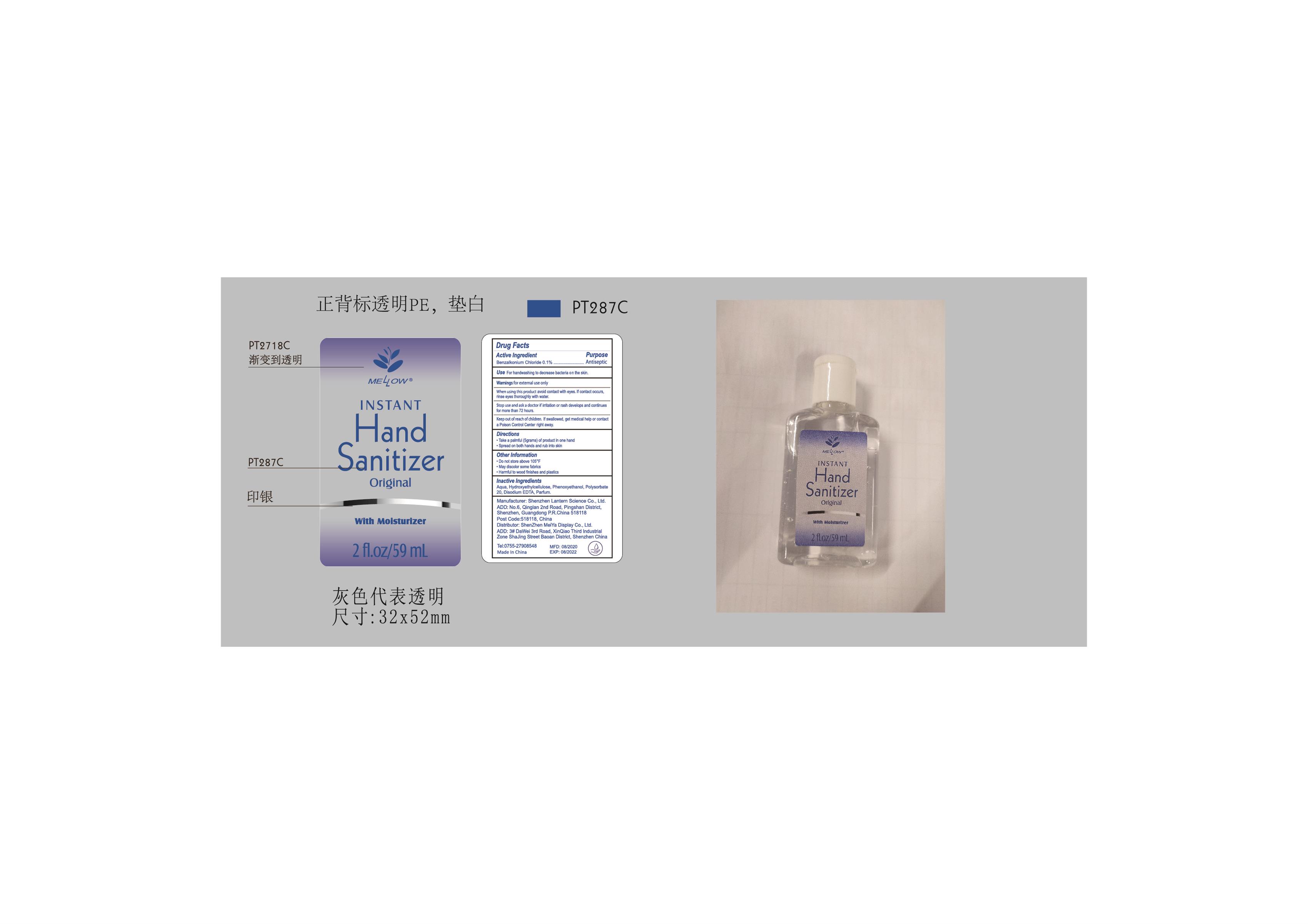 DRUG LABEL: Mellow hand sanitizer 59ml
NDC: 54860-329 | Form: LIQUID
Manufacturer: Shenzhen Lantern Science Co.,Ltd.
Category: otc | Type: HUMAN OTC DRUG LABEL
Date: 20200902

ACTIVE INGREDIENTS: BENZALKONIUM CHLORIDE 0.1 g/100 mL
INACTIVE INGREDIENTS: LEMON 0.05 mL/100 mL; POLYSORBATE 20 0.15 mL/100 mL; WATER 98.3 mL/100 mL; EDETATE DISODIUM ANHYDROUS 0.1 mL/100 mL; HYDROXYETHYL CELLULOSE, UNSPECIFIED 0.9 mL/100 mL; PHENOXYETHANOL 0.4 mL/100 mL

Mellow hand sanitizer 59ml

Active Ingredient

Active Ingredients Purpose

Benzalkonium Chloride 0.1% Antiseptic

Warning

For external use only.

WARNINGS AND PRECAUTIONS

For external use only.

Flammable, keep away from heat and flame.

STOP USE

Discontinue if skin becomes irritated and ask a doctor .

Keep out of reach of children. In case of accidental ingestion, seek professional assistance or contact a poson control center immediately.

Inactive ingredients

Aqua,Hydroxyethylcollulose,Phenoxyethanol,Polysorbate 20,Disodium EDTA,Parfum.

Directions

Take a palmful(5 grams) of product in one hand.

Spread on both hands and rub into skin.

When using this product

keep out of eyes. In case of contact with eyes, flush thoroughly with water.

Do not inhale or ingest.

Avoid contact with broken skin.

Other information

Do not store above 105F.

May discolor some fabrics.

Harmful to wood finishes and plastics.

When using this product

avoid contact with eyes,if contact occurs,rinse eyes thoroughly with water.

Keep out of reach of children

If swallowed,get medical help or contact a Poison Control Center right away.

stop use and ask a doctor if irritation or rash develops and continues for more than 72 hours.

Use

For handwashing to decrease bacteria on the skin.

OTHER SAFETY INFORMATION

Do not store above105℉

May discolor some fabrics

Harmful to wood finishes and plastics.

dosage

take a palmful(5 grams) of product in one hand.

spread on both hands and rub into skin.